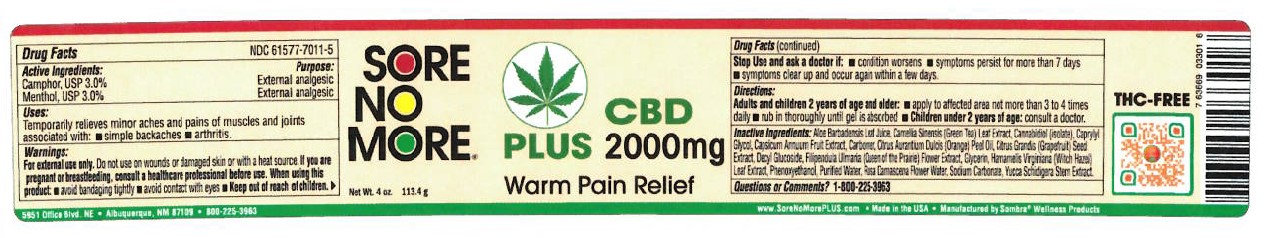 DRUG LABEL: Sore No More Warm Therapry Plus CBD 2000mg
NDC: 61577-7012 | Form: GEL
Manufacturer: SOMBRA COSMETICS INC.
Category: otc | Type: HUMAN OTC DRUG LABEL
Date: 20220523

ACTIVE INGREDIENTS: CAMPHOR (SYNTHETIC) 0.03 g/1 g
INACTIVE INGREDIENTS: ALOE VERA LEAF; CARBOMER HOMOPOLYMER TYPE C; DECYL GALLATE; water; CAPSAICIN; GRAPE SEED OIL; GREEN TEA LEAF; FILIPENDULA ULMARIA FLOWER; ROSA CENTIFOLIA FLOWER OIL; SODIUM CARBONATE; GLYCERIN; WITCH HAZEL; YUCCA SCHIDIGERA ROOT; ORANGE PEEL; CANNABIDIOL; MENTHOL

Sore No More Warm Therapy Plus CBD 2000mg Natural Pain Relieving Gel

ACTIVE INGREDIENTS

MENTHOL USP 3%, CAMPHOR USP 3%

PURPOSE

EXTERNAL ANALGESIC

KEEP OUT OF REACH OF CHILDREN

USES

TEMPORARILY RELIEVES MINOR ACHES AND PAINS OF MUSCLES AND JOINTS ASSOCIATED WITH: SIMPLE BACKACHES

WARNINGS SECTION

FOR EXTERNAL USE ONLY. DO NOT USE ON WOUNDS OR DAMAGED SKIN. WHEN USING THIS PRODUCTS: AVOID BANDAGING TIGHTLY, AVOID CONTACT WITH EYES, KEEP OUT OF REACH OF CHILDREN.

STOP USE AND ASK DOCTOR IF: CONDITION WORENS, SYMPTONS PERSIST FOR MORE THAN 7 DAYS, CLEAR UP AND OCCUR AGAIN WITHIN A FEW DAYS.

DIRECTIONS

ADULTS AND CHILDREN 2 YEARS OF AGE AND OLDER: APPLY TO AFFECTED AREA NOT MORE THAN 3 TO 4 TIMES DAILY, RUB IN THOROUGHLY UNTIL GEL IS ABSORBED, CHILDREN UNDER 2 YEARS OF AGE: CONSULT A DOCTOR.

INACTIVE INGREDIENTS

aloe barbadensis leaf juice, carbomer, decyl glucoside, water, citrus grandis (grapefruit) seed extract, camellia sinensis (green tea) leaf extract, citrus aurantium dulcis (orange) peel oil, spiraea ulmaria flower (queen of the prairie) extract, rosa damascena flower water, sodium carbonate, glycerin, hamamelis virginiana (witch hazel) leaf extract, yucca schidigera root extract, phenoxyethanol, caprylyl glycol, cannabidiol, capsicum annuum fruit extract,

Question or comments

1-800-225-3963